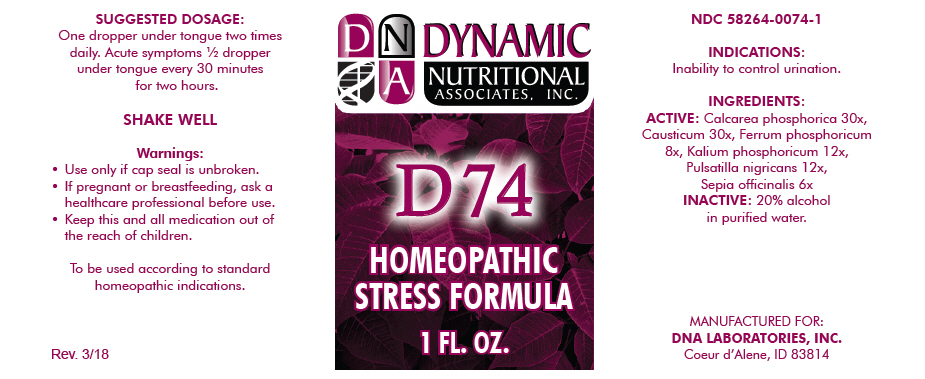 DRUG LABEL: D-74
NDC: 58264-0074 | Form: SOLUTION
Manufacturer: DNA Labs, Inc.
Category: homeopathic | Type: HUMAN OTC DRUG LABEL
Date: 20250113

ACTIVE INGREDIENTS: TRIBASIC CALCIUM PHOSPHATE 30 [hp_X]/1 mL; CAUSTICUM 30 [hp_X]/1 mL; FERROSOFERRIC PHOSPHATE 8 [hp_X]/1 mL; DIBASIC POTASSIUM PHOSPHATE 12 [hp_X]/1 mL; ANEMONE PRATENSIS 12 [hp_X]/1 mL; SEPIA OFFICINALIS JUICE 6 [hp_X]/1 mL
INACTIVE INGREDIENTS: ALCOHOL; WATER

D-74

NDC 58264-0074-1

INDICATIONS

PURPOSE

Inability to control urination.

INGREDIENTS

ACTIVE

Calcarea phosphorica 30x, Causticum 30x, Ferrum phosphoricum 8x, Kalium phosphoricum 12x, Pulsatilla nigricans 12x, Sepia officinalis 6x

INACTIVE

20% alcohol in purified water.

SUGGESTED DOSAGE

One dropper under tongue two times daily. Acute symptoms ½ dropper under tongue every 30 minutes for two hours.

STORAGE AND HANDLING

SHAKE WELL

Warnings

- Use only if cap seal is unbroken.

PREGNANCY OR BREAST FEEDING

- If pregnant or breastfeeding, ask a healthcare professional before use.

KEEP OUT OF REACH OF CHILDREN

- Keep this and all medication out of the reach of children.

To be used according to standard homeopathic indications.

PRINCIPAL DISPLAY PANEL - 1 FL. OZ. Bottle Label

DYNAMIC
NUTRITIONAL
ASSOCIATES, INC.

D 74

HOMEOPATHIC
STRESS FORMULA

1 FL. OZ.